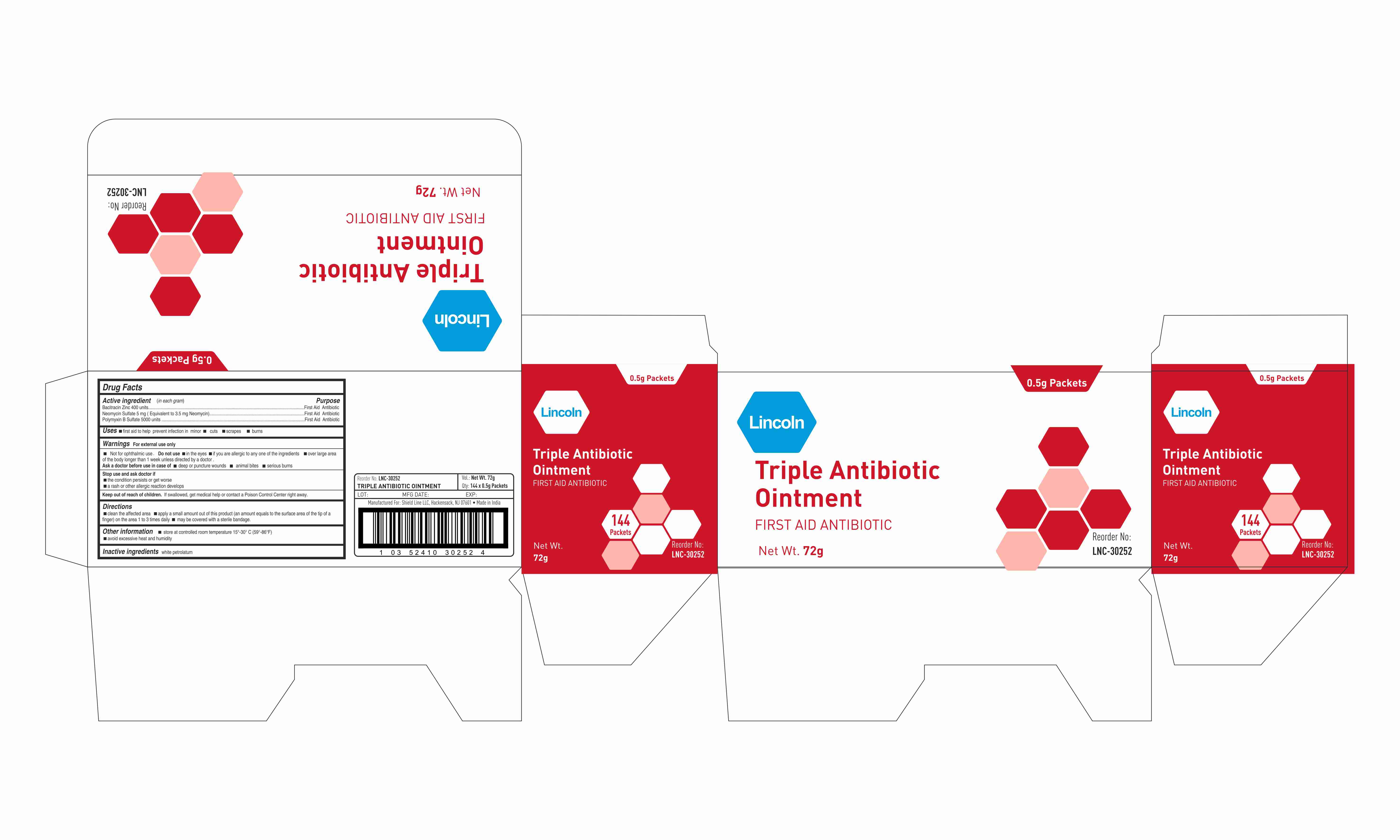 DRUG LABEL: Lincoln
NDC: 69636-3025 | Form: OINTMENT
Manufacturer: Lincoln Pharmaceutical Ltd.
Category: otc | Type: HUMAN OTC DRUG LABEL
Date: 20160408

ACTIVE INGREDIENTS: POLYMYXIN B SULFATE 5000 [USP'U]/1 g; NEOMYCIN SULFATE 3.5 mg/1 g; BACITRACIN ZINC 400 [USP'U]/1 g
INACTIVE INGREDIENTS: PETROLATUM

Drug Facts

Bacitracin Zinc 400 units- Neomycin Sulfate 5 mg (Equivalent to 3.5 mg Neomycin) Polymyxin B sulfate 5000 units

Drug Facts

First Aid antibiotic

Drug Facts

Uses

- First aid to prevent infection in
- minor cuts
- scrapes
- burns

Drug Facts

For External use only

Drug Facts

- in the eyes
- if you are allergenic to any of the ingredients
- over the large areas of the body
- longer than 1 week unless directed by a doctor

Drug Facts

- deep or puncture wounds
- animal bites
- serious burns

Drug Facts

- the condition persists or get worse
- a rash or other allergic reaction develops

Drug Facts

If swallowed, get medical help or contact a Poison Control Center right away.

Drug Facts

- clean the affected area
- apply a small amount of this product (an amount equal to the surface area of the tip of a finger) on the area 1 to 3 times daily
- may be covered with sterile bandage

OTHER SAFETY INFORMATION

- store at room temperature 15- 30° C (59-86F)
- avoid excessive heat and humidity

Drug Facts

white petrolatum